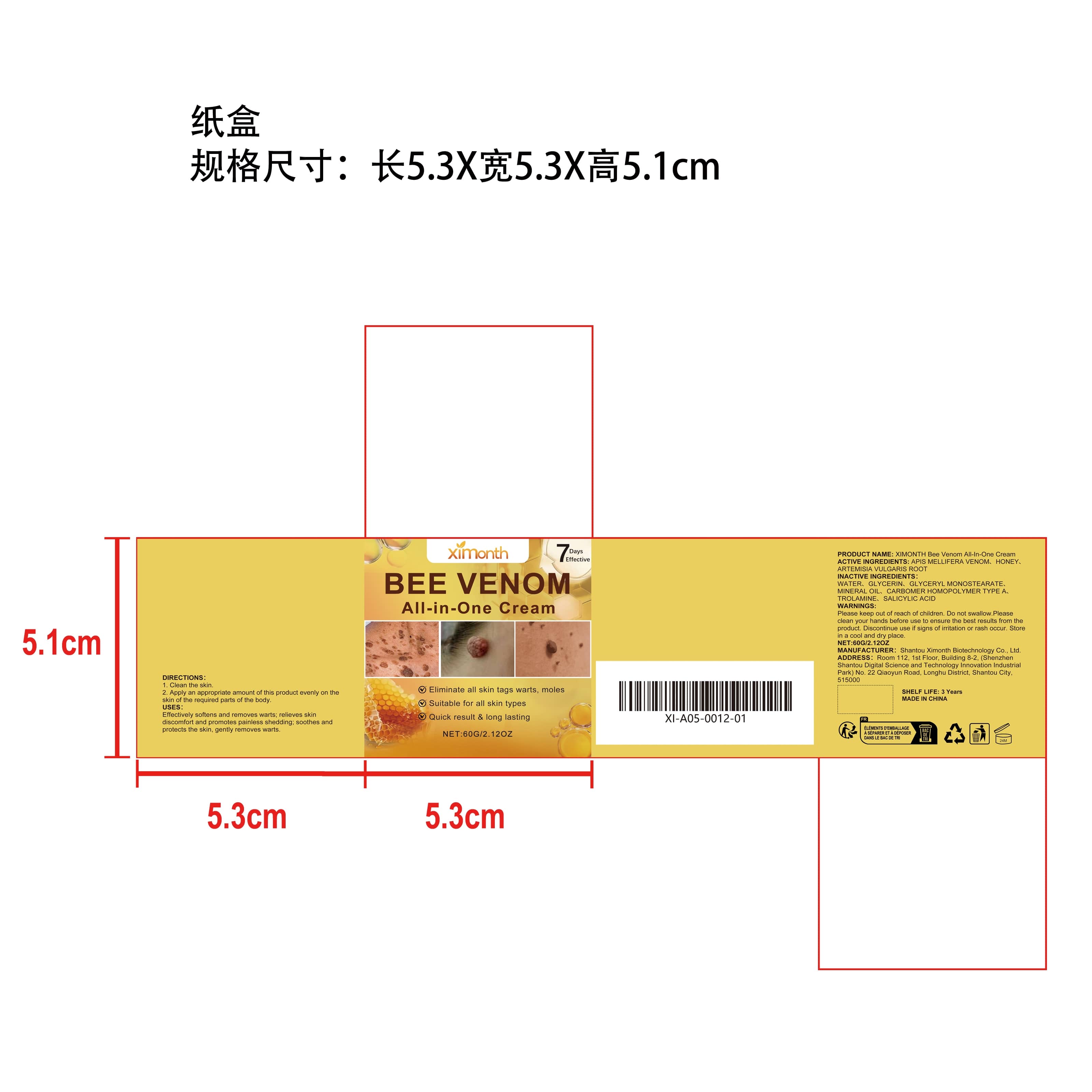 DRUG LABEL: XIMONTH Bee Venom All-In-One Cream
NDC: 84989-013 | Form: CREAM
Manufacturer: Shantou Ximonth Biotechnology Co., Ltd.
Category: otc | Type: HUMAN OTC DRUG LABEL
Date: 20251204

ACTIVE INGREDIENTS: ARTEMISIA VULGARIS ROOT 0.012 mg/60 mg; APIS MELLIFERA VENOM 0.012 mg/60 mg; HONEY 0.012 mg/60 mg
INACTIVE INGREDIENTS: GLYCERIN 4.8 mg/60 mg; GLYCERYL MONOSTEARATE 0.6 mg/60 mg; SALICYLIC ACID 0.012 mg/60 mg; TROLAMINE 0.12 mg/60 mg; WATER 53.712 mg/60 mg; CARBOMER HOMOPOLYMER TYPE A 0.12 mg/60 mg; MINERAL OIL 0.6 mg/60 mg

ACTIVE INGREDIENT

APIS MELLIFERA VENOM、HONEY、ARTEMISIA VULGARIS ROOT

PURPOSE

Effectively softens and removes warts; relieves skin discomfort and promotes painless shedding; soothes and protects the skin, gently removes warts.

WHEN USING

1. Clean the skin.

2. Apply an appropriate amount of this product evenly on the skin of the required parts of the body.

WARNINGS

Please keep out of reach of children. Do not swallow.Please clean your hands before use to ensure the best results from the product. Discontinue use if signs of irritation or rash occur. Store in a cool and dry place.

DO NOT USE

Discontinue use if signs of irritation or rash occur.

STOP USE

Discontinue use if signs of irritation or rash occur.

KEEP OUT OF REACH OF CHILDREN

Please keep out of reach of children. Do not swallow.

STORAGE AND HANDLING

Store in a cool and dry place.

INACTIVE INGREDIENT

WATER、GLYCERIN、GLYCERYL MONOSTEARATE、MINERAL OIL、CARBOMER HOMOPOLYMER TYPE A、TROLAMINE、SALICYLIC ACID

INDICATIONS AND USAGE

1. Clean the skin.

2. Apply an appropriate amount of this product evenly on the skin of the required parts of the body.

DOSAGE AND ADMINISTRATION

1. Clean the skin.

2. Apply an appropriate amount of this product evenly on the skin of the required parts of the body.